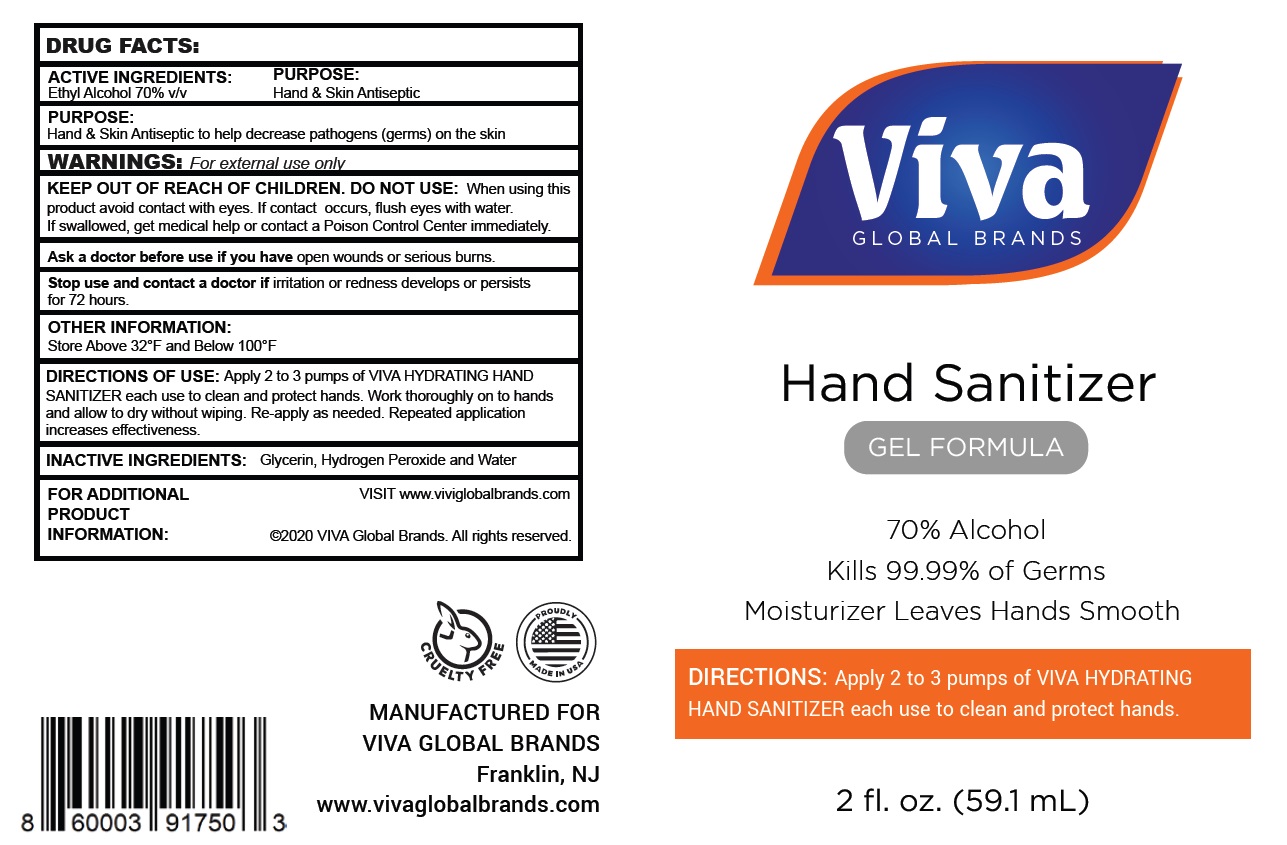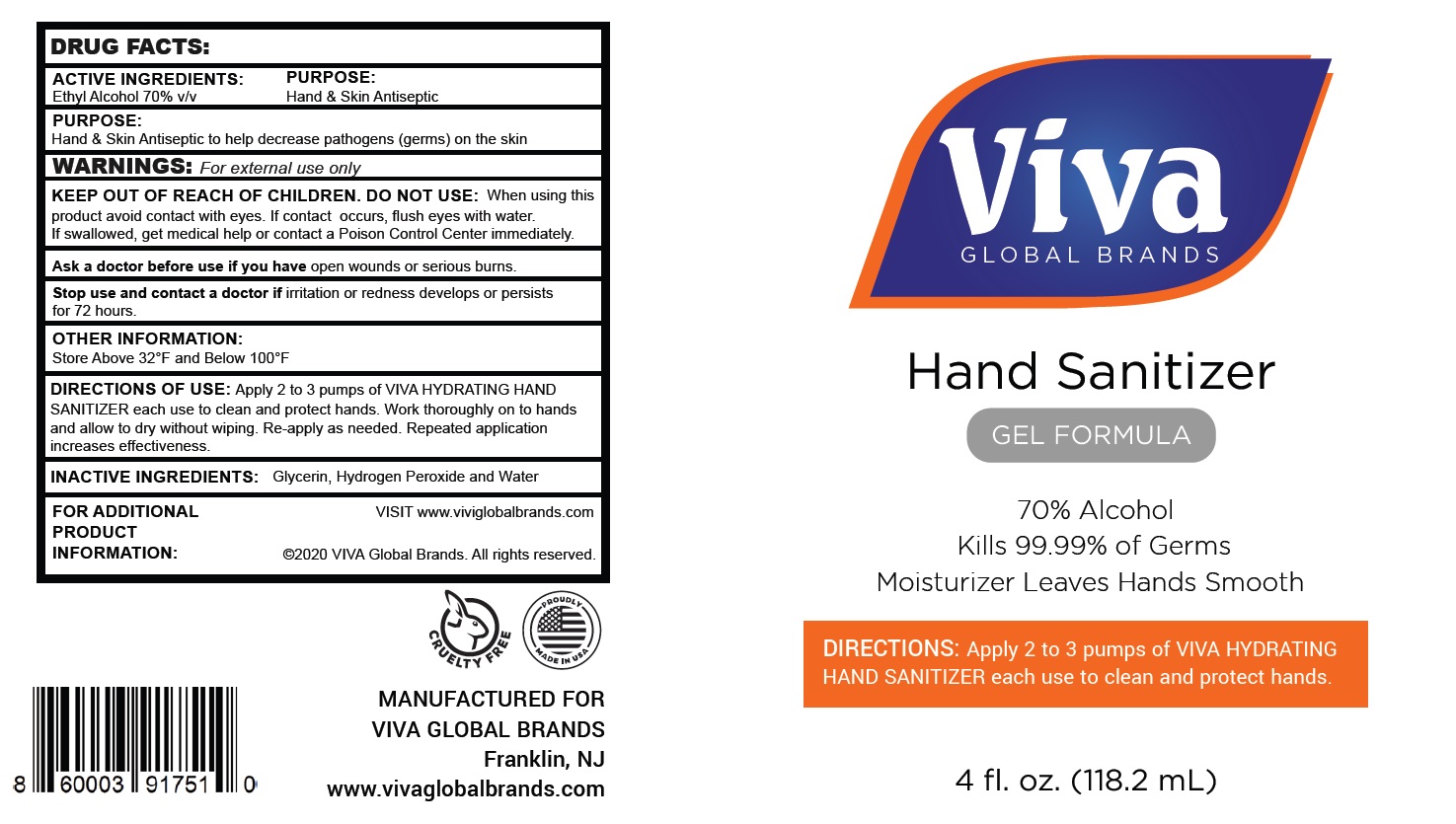 DRUG LABEL: VIVA
NDC: 76549-072 | Form: GEL
Manufacturer: Viva Products
Category: otc | Type: HUMAN OTC DRUG LABEL
Date: 20200604

ACTIVE INGREDIENTS: ALCOHOL 70 mL/100 mL
INACTIVE INGREDIENTS: WATER; GLYCERIN; HYDROGEN PEROXIDE

Active Ingredient

Ethyl Alcohol 70% v/v.

Purpose

Hand & Skin Antiseptic

Use

Hand & Skin Antiseptic to help decrease pathogens (germs) on the skin

Warnings

For external use only.

When using this product

avoid contact with eyes. If contact occurs, flush eyes with water.

KEEP OUT OF REACH OF CHILDREN.

If swallowed, get medical help or contact a Poison Control Center immediately.

Ask a doctor before use if you have

open wounds or serious burns.

Stop use and contact a doctor if

irritation or redness develops or persists for 72 hours.

Directions

Apply 2 to 3 pumps of VIVA HYDRATIN HAND SANITIZER each use to clean and protect hands. Work thoroughly on to hands and allow to dry without wiping. Re-apply as needed. Repeated application increases effectiveness.

Storage

Store Above 32°F and Below 100°F

Inactive ingredients

Glycerin, Hydrogen Peroxide and Water

Additional Information

FOR ADDITIONAL PRODUCT INFORMATION: VISIT www.viviglobalbrands.com

Principal Display Panel

NDC 76549-072-01, 76549-072-02, 76549-072-03, 76549-072-04, 76549-072-08, 76549-072-09, 76549-072-16, 76549-072-37

VIVA GLOBAL BRANDS

HAND SANITIZER

GEL FORMULA

70% Alcohol

Kills 99.99% of Germs

Moisturizer Leaves Hands Smooth

DIRECTIONS: Apply 2 to 3 pumps of VIVA HYDRATING HAND SANITIZER each use to clean and protect hands.

1.7 FL OZ (50 mL)

2 FL OZ (59.1 mL)

3.4 FL OZ (100 mL)

4 FL OZ (118.2 mL)

8 FL OZ (236.6 mL)

8.5 FL OZ (251 mL)

16 FL OZ (473 mL)

1 Gallon (3785 mL)